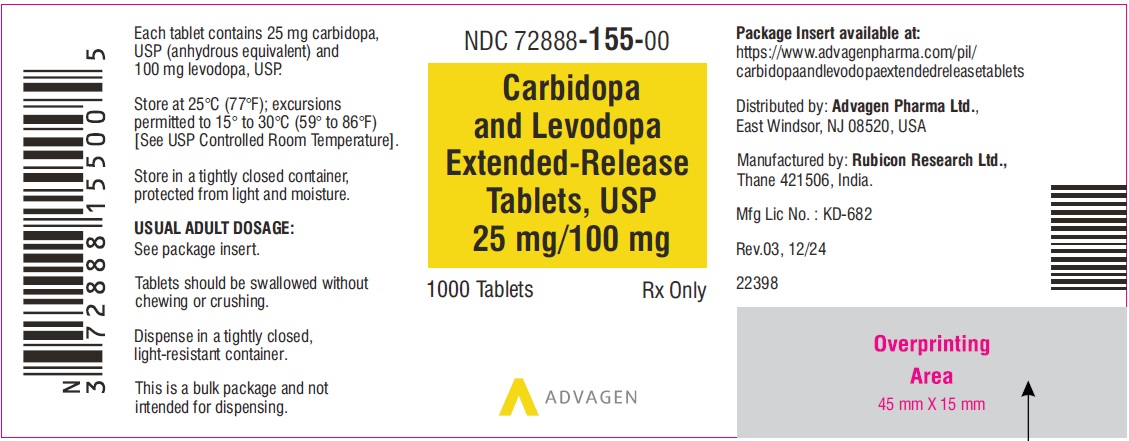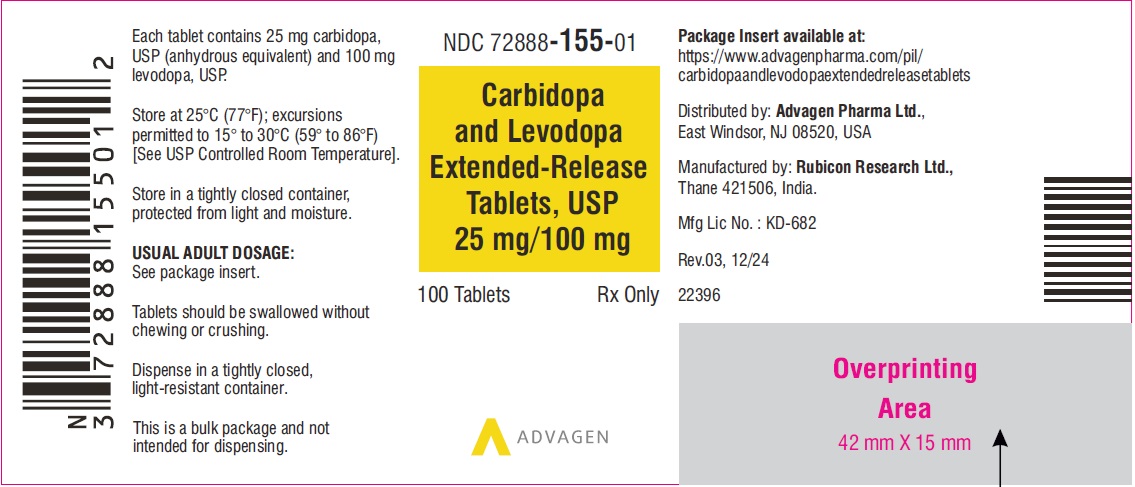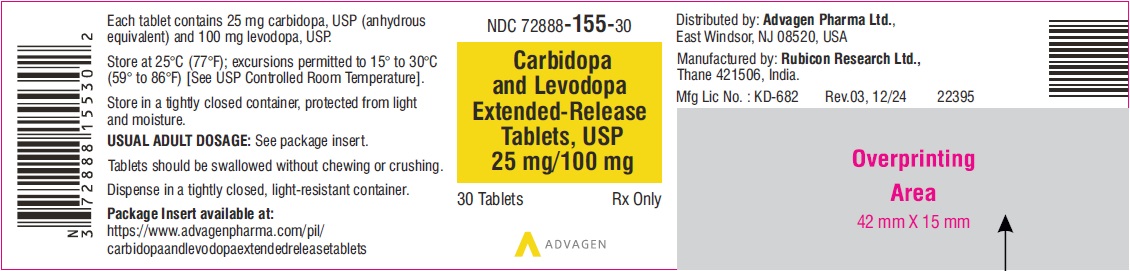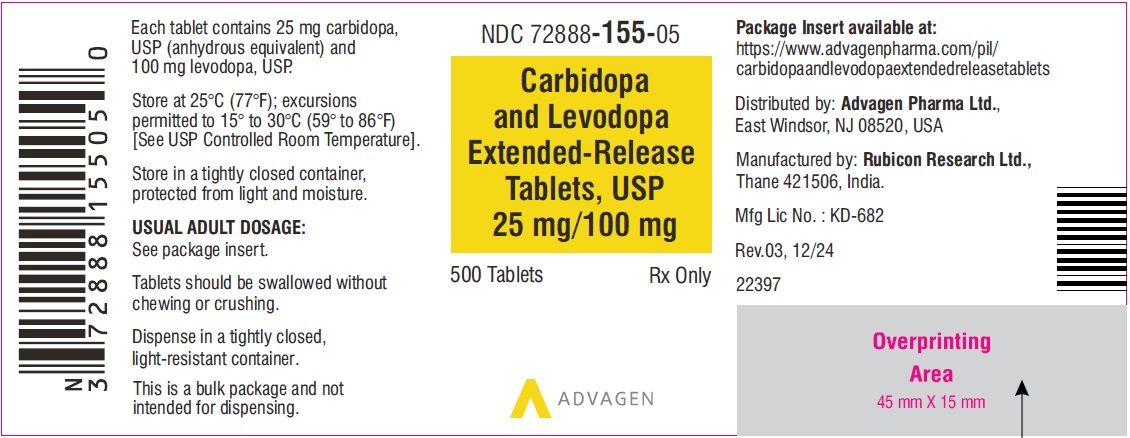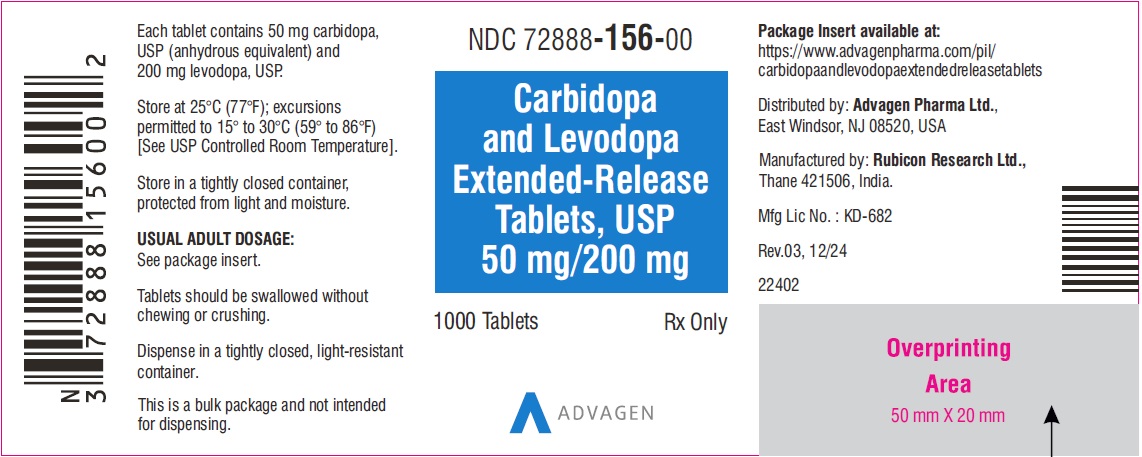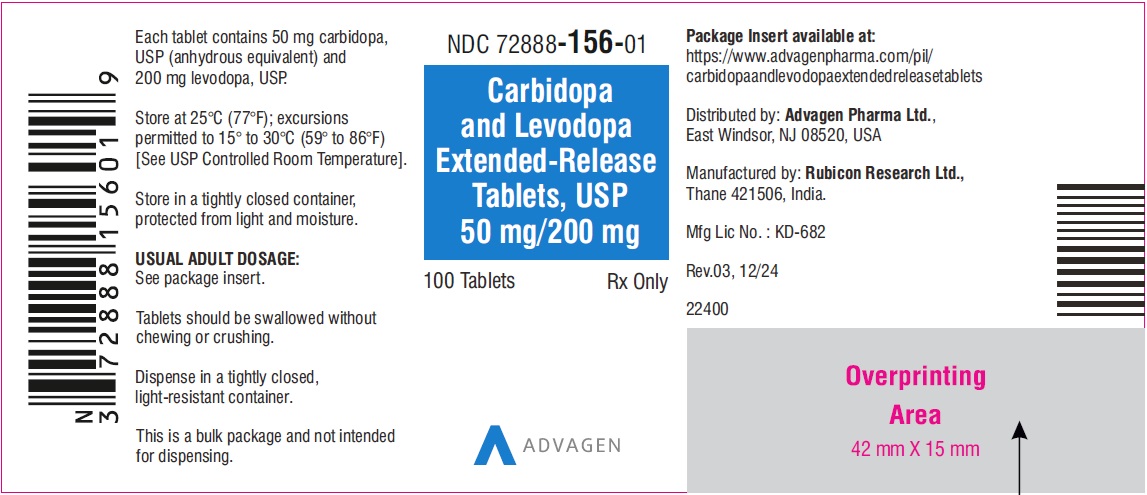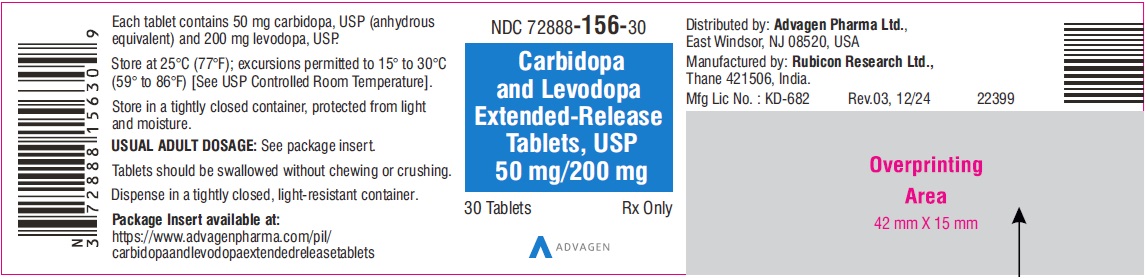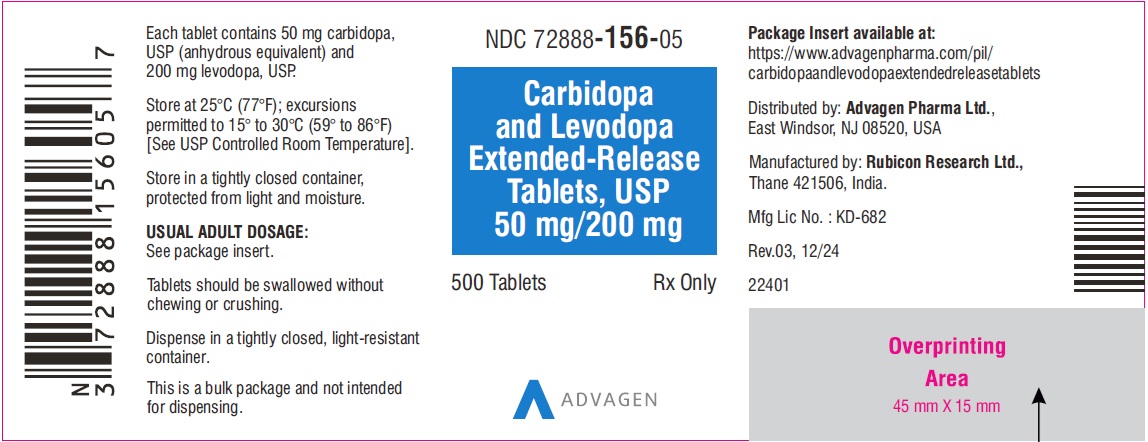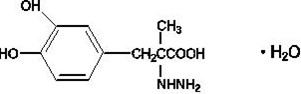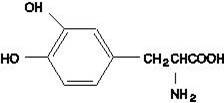 DRUG LABEL: Carbidopa and levodopa
NDC: 72888-155 | Form: TABLET, EXTENDED RELEASE
Manufacturer: Advagen Pharma Ltd
Category: prescription | Type: HUMAN PRESCRIPTION DRUG LABEL
Date: 20251204

ACTIVE INGREDIENTS: CARBIDOPA 25 mg/1 1; LEVODOPA 100 mg/1 1
INACTIVE INGREDIENTS: HYDROXYPROPYL CELLULOSE, UNSPECIFIED; HYPROMELLOSE, UNSPECIFIED; MICROCRYSTALLINE CELLULOSE; MAGNESIUM STEARATE; SILICON DIOXIDE; FD&C RED NO. 40; FD&C BLUE NO. 2--ALUMINUM LAKE

Carbidopa and Levodopa Extended-Release Tablets, USP

DESCRIPTION

Carbidopa and Levodopa extended-release tablets, USP are extended-release oral dosage form and are combination of carbidopa and levodopa for the treatment of Parkinson's disease and syndrome.

Carbidopa, an inhibitor of aromatic amino acid decarboxylation, is a white, crystalline compound, slightly soluble in water, with a molecular weight of 244.3. It is designated chemically as (-)-L-α-hydrazino- α -methyl-β-(3,4-dihydroxybenzene) propanoic acid monohydrate. Its empirical formula is C10H14N2O4•H2O, and its structural formula is:

Tablet content is expressed in terms of anhydrous carbidopa, which has a molecular weight of 226.3.

Levodopa, an aromatic amino acid, is a white, crystalline compound, slightly soluble in water, with a molecular weight of 197.2. It is designated chemically as (-)-L- α -amino- β -(3,4-dihydroxybenzene) propanoic acid. Its empirical formula is C9H11NO4, and its structural formula is:

Carbidopa and levodopa extended-release tablets, USP are supplied as extended-release tablets containing either 50 mg of carbidopa and 200 mg of levodopa, or 25 mg of carbidopa and 100 mg of levodopa. Inactive ingredients are hydroxypropyl cellulose, hypromellose, microcrystalline cellulose, magnesium stearate, and colloidal silicon dioxide. Carbidopa and levodopa extended-release tablets, USP 25 mg/100 mg and 50 mg/ 200 mg also contain FD&C red 40 Alu lake and FD&C blue 2 Alu lake.

The 25 mg/100 mg tablet is supplied as light purple to purple, dappled, oval, uncoated tablets, debossed with “Λ50” on one side and plain on other. The 50 mg/200 mg tablet is supplied as light purple to purple, dappled, oval, uncoated tablets, debossed with “Λ51” on one side and plain on other. Carbidopa and levodopa extended-release tablets are polymeric-based drug delivery system that controls the release of carbidopa and levodopa as it slowly erodes. Carbidopa and levodopa extended-release tablets 25 mg/100 mg are available to facilitate titration when 100 mg steps are required.

FDA approved dissolution test specifications differ from USP.

CLINICAL PHARMACOLOGY

Mechanism of Action

Parkinson's disease is a progressive, neurodegenerative disorder of the extrapyramidal nervous system affecting the mobility and control of the skeletal muscular system. Its characteristic features include resting tremor, rigidity, and bradykinetic movements. Symptomatic treatments, such as levodopa therapies, may permit the patient better mobility.

Current evidence indicates that symptoms of Parkinson's disease are related to depletion of dopamine in the corpus striatum. Administration of dopamine is ineffective in the treatment of Parkinson's disease apparently because it does not cross the blood-brain barrier. However, levodopa, the metabolic precursor of dopamine, does cross the blood-brain barrier, and presumably is converted to dopamine in the brain. This is thought to be the mechanism whereby levodopa relieves symptoms of Parkinson's disease.

Pharmacodynamics

When levodopa is administered orally, it is rapidly decarboxylated to dopamine in extracerebral tissues so that only a small portion of a given dose is transported unchanged to the central nervous system. For this reason, large doses of levodopa are required for adequate therapeutic effect, and these may often be accompanied by nausea and other adverse reactions, some of which are attributable to dopamine formed in extracerebral tissues.

Since levodopa competes with certain amino acids for transport across the gut wall, the absorption of levodopa may be impaired in some patients on a high protein diet.

Carbidopa inhibits decarboxylation of peripheral levodopa. It does not cross the blood-brain barrier and does not affect the metabolism of levodopa within the central nervous system.

Since its decarboxylase inhibiting activity is limited to extracerebral tissues, administration of carbidopa with levodopa makes more levodopa available for transport to the brain.

Patients treated with levodopa therapy for Parkinson's disease may develop motor fluctuations characterized by end-of-dose failure, peak dose dyskinesia, and akinesia. The advanced form of motor fluctuations (‘on-off’ phenomenon) is characterized by unpredictable swings from mobility to immobility. Although the causes of the motor fluctuations are not completely understood, in some patients they may be attenuated by treatment regimens that produce steady plasma levels of levodopa.

Carbidopa and levodopa extended-release tablets contains either 50 mg of carbidopa and 200 mg of levodopa, or 25 mg of carbidopa and 100 mg of levodopa in an extended-release dosage form designed to release these ingredients over a 4-to 6-hour period. With carbidopa and levodopa extended-release tablets there is less variation in plasma levodopa levels than with carbidopa and levodopa immediate release tablets, the conventional formulation. However, carbidopa and levodopa extended-release tablets are less systemically bioavailable than carbidopa and levodopa tablets and may require increased daily doses to achieve the same level of symptomatic relief as provided by carbidopa and levodopa tablets.

In clinical trials, patients with moderate to severe motor fluctuations who received carbidopa and levodopa extended-release tablets did not experience quantitatively significant reductionsin ‘off’ time when compared to carbidopa and levodopa tablets. However, global ratings of improvement as assessed by both patient and physician were better during therapy with carbidopa and levodopa extended-release tablets than with carbidopa and levodopa tablets. In patients without motor fluctuations, carbidopa and levodopa extended-release tablets, under controlled conditions, provided the same therapeutic benefit with less frequent dosing when compared to carbidopa and levodopa tablets.

Pharmacokinetics

Carbidopa reduces the amount of levodopa required to produce a given response by about 75% and, when administered with levodopa, increases both plasma levels and the plasma half-life of levodopa, and decreases plasma and urinary dopamine and homovanillic acid.

Elimination half-life of levodopa in the presence of carbidopa is about 1.5 hours. Following carbidopa and levodopa extended-release tablets, the apparent half-life of levodopa may be prolonged because of continuous absorption.

In healthy elderly subjects (56-67 years old) the mean time-to-peak concentration of levodopa after a single dose of carbidopa and levodopa extended-release tablets 50mg/200mg was about 2 hours as compared to 0.5 hours after standard carbidopa and levodopa tablets. The maximum concentration of levodopa after a single dose of carbidopa and levodopa extended-release tablets was about 35% of the standard carbidopa and levodopa tablets (1151 vs. 3256 ng/mL). The extent of availability of levodopa from carbidopa and levodopa extended-release tablets was about 70-75% relative to intravenous levodopa or standard carbidopa and levodopa tablets in the elderly. The absolute bioavailability of levodopa from carbidopa and levodopa extended-release tablets (relative to I.V.) in young subjects was shown to be only about 44%. The extent of availability and the peak concentrations of levodopa were comparable in the elderly after a single dose and at steady state after t.i.d. administration of carbidopa and levodopa extended-release tablets 50mg/200mg. In elderly subjects, the average trough levels of levodopa at steady state after the extended-release tablet were about 2 fold higher than after the standard carbidopa and levodopa tablets (163 vs. 74 ng/mL).

In these studies, using similar total daily doses of levodopa, plasma levodopa concentrations with carbidopa and levodopa extended-release tablets fluctuated in a narrower range than with carbidopa and levodopa tablets. Because the bioavailability of levodopa from carbidopa and levodopa extended-release tablets relative to carbidopa and levodopa tablets is approximately 70-75%, the daily dosage of levodopa necessary to produce a given clinical response with the sustained-release formulation will usually be higher.

The extent of availability and peak concentrations of levodopa after a single dose of carbidopa and levodopa extended-release tablets 50 mg/200 mg increased by about 50% and 25%, respectively, when administered with food.

At steady state, the bioavailability of carbidopa from carbidopa and levodopa tablets is approximately 99% relative to the concomitant administration of carbidopa and levodopa. At steady state, carbidopa bioavailability from carbidopa and levodopa extended-release tablets 50 mg/200 mg is approximately 58% relative to that from carbidopa and levodopa tablets.

Pyridoxine hydrochloride (vitamin B6), in oral doses of 10 mg to 25 mg, may reverse the effects of levodopa by increasing the rate of aromatic amino acid decarboxylation. Carbidopa inhibits this action of pyridoxine.

Special Populations

Geriatric:A study in eight young healthy subjects (21-22 yr) and eight elderly healthy subjects (69-76 yr) showed that the absolute bioavailability of levodopa was similar between young and elderly subjects following oral administration of levodopa and carbidopa. However, the systemic exposure (AUC) of levodopa was increased by 55% in elderly subjects compared to young subjects. Based on another study in forty patients with Parkinson’s disease, there was a correlation between age of patients and the increase of AUC of levodopa following administration of levodopa and an inhibitor of peripheral dopa decarboxylase. AUC of levodopa was increased by 28% in elderly patients (≥ 65 yr) compared to young patients (< 65 yr). Additionally, mean value of Cmaxfor levodopa was increased by 24% in elderly patients (≥ 65 yr) compared to young patients (< 65 yr) (see PRECAUTIONS, Geriatric Use).

The AUC of carbidopa was increased in elderly subjects (n=10, 65-76 yr) by 29% compared to young subjects (n=24, 23-64 yr) following IV administration of 50 mg levodopa with carbidopa (50 mg). This increase is not considered a clinically significant impact.

INDICATIONS AND USAGE

Carbidopa and levodopa extended-release tablets are indicated in the treatment of Parkinson's disease, post-encephalitic parkinsonism, and symptomatic parkinsonism that may follow carbon monoxide intoxication or manganese intoxication.

CONTRAINDICATIONS

Nonselective monoamine oxidase (MAO) inhibitors are contraindicated for use with carbidopa and levodopa extended-release tablets. These inhibitors must be discontinued at least two weeks prior to initiating therapy with carbidopa and levodopa extended-release tablets. Carbidopa and levodopa extended-release tablets may be administered concomitantly with the manufacturer's recommended dose of an MAO inhibitor with selectivity for MAO type B (e.g., selegiline HCl) (see PRECAUTIONS, Drug Interactions).

carbidopa and levodopa extended-release tablets are contraindicated in patients with known hypersensitivity to any component of this drug, and in patients with narrow-angle glaucoma.

WARNINGS

When patients are receiving levodopa without a decarboxylase inhibitor, levodopa must be discontinued at least twelve hours before carbidopa and levodopa extended-release tablets are started. In order to reduce adverse reactions, it is necessary to individualize therapy. See DOSAGE AND ADMINISTRATIONsection before initiating therapy.

Carbidopa and levodopa extended-release tablets should be substituted at a dosage that will provide approximately 25% of the previous levodopa dosage (see DOSAGE AND ADMINISTRATION).

Carbidopa does not decrease adverse reactions due to central effects of levodopa. By permitting more levodopa to reach the brain, particularly when nausea and vomiting is not a dose-limiting factor, certain adverse central nervous system (CNS) effects, e.g., dyskinesias, will occur at lower dosages and sooner during therapy with carbidopa and levodopa extended-release tablets than with levodopa alone.

Patients receiving carbidopa and levodopa extended-release tablets may develop increased dyskinesias compared to carbidopa and levodopa tablets. Dyskinesias are a common side effect of carbidopa levodopa treatment. The occurrence of dyskinesias may require dosage reduction.

All patients should be observed carefully for the development of depression with concomitant suicidal tendencies.

Carbidopa and levodopa extended-release tablets should be administered cautiously to patients with severe cardiovascular or pulmonary disease, bronchial asthma, renal, hepatic or endocrine disease.

As with levodopa, care should be exercised in administering carbidopa and levodopa extended-release tablets to patients with a history of myocardial infarction who have residual atrial, nodal, or ventricular arrhythmias. In such patients, cardiac function should be monitored with particular care during the period of initial dosage adjustment, in a facility with provisions for intensive cardiac care.

As with levodopa, treatment with carbidopa and levodopa extended-release tablets may increase the possibility of upper gastrointestinal hemorrhage in patients with a history of peptic ulcer.

Falling Asleep During Activities of Daily Living and Somnolence

Patients taking carbidopa and levodopa extended-release tablets alone or with other dopaminergic drugs have reported suddenly falling asleep without prior warning of sleepiness while engaged in activities of daily living (includes operation of motor vehicles). Road traffic accidents attributed to sudden sleep onset have been reported. Although many patients reported somnolence while on dopaminergic medications, there have been reports of road traffic accidents attributed to sudden onset of sleep in which the patient did not perceive any warning signs, such as excessive drowsiness, and believed that they were alert immediately prior to the event. Sudden onset of sleep has been reported to occur as long as one year after the initiation of treatment.

Falling asleep while engaged in activities of daily living usually occurs in patients experiencing pre- existing somnolence, although some patients may not give such a history. For this reason, prescribers should reassess patients for drowsiness or sleepiness especially since some of the events occur well after the start of treatment. Prescribers should be aware that patients may not acknowledge drowsiness or sleepiness until directly questioned about drowsiness or sleepiness during specific activities. Patients should be advised to exercise caution while driving or operating machines during treatment with carbidopa and levodopa extended-release tablets. Patients who have already experienced somnolence or an episode of sudden sleep onset should not participate in these activities during treatment with carbidopa and levodopa extended-release tablets.

Before initiating treatment with carbidopa and levodopa extended-release tablets, advise patients about the potential to develop drowsiness and ask specifically about factors that may increase the risk for somnolence with carbidopa and levodopa extended-release tablets such as the use of concomitant sedating medications and the presence of sleep disorders. Consider discontinuing carbidopa and levodopa extended-release tablets in patients who report significant daytime sleepiness or episodes of falling asleep during activities that require active participation (e.g., conversations, eating, etc.). If treatment with carbidopa and levodopa extended-release tablets continues, patients should be advised not to drive and to avoid other potentially dangerous activities that might result in harm if the patients become somnolent. There is insufficient information to establish that dose reduction will eliminate episodes of falling asleep while engaged in activities of daily living.

Hyperpyrexia and Confusion

Sporadic cases of a symptom complex resembling neuroleptic malignant syndrome (NMS) have been reported in association with dose reductions or withdrawal of certain antiparkinsonian agents such as levodopa, carbidopa levodopa and carbidopa levodopa extended release. Therefore, patients should be observed carefully when the dosage of levodopa is reduced abruptly or discontinued, especially if the patient is receiving neuroleptics.

NMS is an uncommon but life-threatening syndrome characterized by fever or hyperthermia. Neurological findings, including muscle rigidity, involuntary movements, altered consciousness, mental status changes; other disturbances, such as autonomic dysfunction, tachycardia, tachypnea, sweating, hyper- or hypotension; laboratory findings, such as creatine phosphokinase elevation, leukocytosis, myoglobinuria, and increased serum myoglobin have been reported.

The early diagnosis of this condition is important for the appropriate management of these patients. Considering NMS as a possible diagnosis and ruling out other acute illnesses (e.g., pneumonia, systemic infection, etc.) is essential. This may be especially complex if the clinical presentation includes both serious medical illness and untreated or inadequately treated extrapyramidal signs and symptoms (EPS). Other important considerations in the differential diagnosis include central anticholinergic toxicity, heat stroke, drug fever, and primary central nervous system (CNS) pathology.

The management of NMS should include: 1) intensive symptomatic treatment and medical monitoring and 2) treatment of any concomitant serious medical problems for which specific treatments are available. Dopamine agonists, such as bromocriptine, and muscle relaxants, such as dantrolene, are often used in the treatment of NMS; however, their effectiveness has not been demonstrated in controlled studies.

PRECAUTIONS

General

As with levodopa, periodic evaluations of hepatic, hematopoietic, cardiovascular, and renal function are recommended during extended therapy.

Patients with chronic wide-angle glaucoma may be treated cautiously with carbidopa and levodopa extended-release tablets provided the intraocular pressure is well-controlled and the patient is monitored carefully for changes in intraocular pressure during therapy.

Dyskinesia

Levodopa alone, as well as carbidopa and levodopa extended-release tablets, is associated with dyskinesias. The occurrence of dyskinesias may require dosage reduction.

Hallucinations / Psychotic-Like Behavior

Hallucinations and psychotic-like behavior have been reported with dopaminergic medications. In general, hallucinations present shortly after the initiation of therapy and may be responsive to dose reduction in levodopa. Hallucinations may be accompanied by confusion and to a lesser extent sleep disorder (insomnia) and excessive dreaming.

Carbidopa and levodopa extended-release tablets may have similar effects on thinking and behavior. This abnormal thinking and behavior may present with one or more symptoms, including paranoid ideation, delusions, hallucinations, confusion, psychotic-like behavior, disorientation, aggressive behavior, agitation, and delirium.

Ordinarily, patients with a major psychotic disorder should not be treated with carbidopa and levodopa extended-release tablets, because of the risk of exacerbating psychosis. In addition, certain medications used to treat psychosis may exacerbate the symptoms of Parkinson’s disease and may decrease the effectiveness of carbidopa and levodopa extended-release tablets.

Impulse Control / Compulsive Behaviors

Reports of patients taking dopaminergic medications (medications that increase central dopaminergic tone), suggest that patients may experience an intense urge to gamble, increased sexual urges, intense urges to spend money, binge eating, and/or other intense urges, and the inability to control these urges. In some cases, although not all, these urges were reported to have stopped when the dose was reduced or the medication was discontinued. Because patients may not recognize these behaviors as abnormal, it is important for prescribers to specifically ask patients or the caregivers about the development of new or increased gambling urges, sexual urges, uncontrolled spending or other urges while being treated with carbidopa and levodopa extended-release tablets. Physicians should consider dose reduction or stopping the medication if a patient develops such urges while taking carbidopa and levodopa extended-release tablets [see Information for Patients].

Melanoma

Epidemiological studies have shown that patients with Parkinson’s disease have a higher risk (2- to approximately 6-fold higher) of developing melanoma than the general population. Whether the increased risk observed was due to Parkinson’s disease or other factors, such as drugs used to treat Parkinson’s disease, is unclear.

For the reasons stated above, patients and providers are advised to monitor for melanomas frequently and on a regular basis when using carbidopa and levodopa extended-release tablets for any indication. Ideally, periodic skin examinations should be performed by appropriately qualified individuals (e.g., dermatologists).

Information for Patients

The patient should be informed that carbidopa and levodopa extended-release tablet is an extended-release formulation of carbidopa levodopa which releases these ingredients over a 4- to 6-hour period. It is important that carbidopa and levodopa extended-release tablets be taken at regular intervals according to the schedule outlined by the physician. The patient should be cautioned not to change the prescribed dosage regimen and not to add any additional antiparkinson medications, including other carbidopa levodopa preparations, without first consulting the physician.

If abnormal involuntary movements appear or get worse during treatment with carbidopa and levodopa extended-release tablets, the physician should be notified, as dosage adjustment may be necessary.

Patients should be advised that sometimes the onset of effect of the first morning dose of carbidopa and levodopa extended-release tablets may be delayed for up to 1 hour compared with the response usually obtained from the first morning dose of carbidopa and levodopa tablets. The physician should be notified if such delayed responses pose a problem in treatment.

Patients should be advised that, occasionally, dark color (red, brown, or black) may appear in saliva, urine, or sweat after ingestion of carbidopa and levodopa extended-release tablets. Although the color appears to be clinically insignificant, garments may become discolored.

The patient should be informed that a change in diet to foods that are high in protein may delay the absorption of levodopa and may reduce the amount taken up in the circulation. Excessive acidity also delays stomach emptying, thus delaying the absorption of levodopa. Iron salts (such as in multivitamin tablets) may also reduce the amount of levodopa available to the body. The above factors may reduce the clinical effectiveness of the levodopa or carbidopa levodopa therapy.

Patients must be advised that the whole or half tablet should be swallowed without chewing or crushing.

Patients should be alerted to the possibility of sudden onset of sleep during daily activities, in some cases without awareness or warning signs, when they are taking dopaminergic agents, including levodopa. Patients should be advised to exercise caution while driving or operating machinery and that if they have experienced somnolence and/or sudden sleep onset, they must refrain from these activities. (See WARNINGS, Falling Asleep During Activities of Daily Living and Somnolence.)

There have been reports of patients experiencing intense urges to gamble, increased sexual urges, and other intense urges, and the inability to control these urges while taking one or more of the medications that increase central dopaminergic tone and that are generally used for the treatment of Parkinson’s disease, including carbidopa and levodopa extended-release tablets. Although it is not proven that the medications caused these events, these urges were reported to have stopped in some cases when the dose was reduced or the medication was stopped. Prescribers should ask patients about the development of new or increased gambling urges, sexual urges or other urges while being treated with carbidopa and levodopa extended-release tablets. Patients should inform their physician if they experience new or increased gambling urges, increased sexual urges, or other intense urges while taking carbidopa and levodopa extended-release tablets. Physicians should consider dose reduction or stopping the medication if a patient develops such urges while taking carbidopa and levodopa extended-release tablets. (See PRECAUTIONS, Impulse Control / Compulsive Behaviors).

Laboratory Tests

Abnormalities in laboratory tests may include elevations of liver function tests such as alkaline phosphatase, SGOT (AST), SGPT (ALT), lactic dehydrogenase (LDH), and bilirubin. Abnormalities in blood urea nitrogen (BUN) and positive Coombs test have also been reported. Commonly, levels of blood urea nitrogen, creatinine, and uric acid are lower during administration of carbidopa levodopa preparations than with levodopa.

Carbidopa levodopa preparations, such as carbidopa and levodopa tablets and carbidopa and levodopa extended-release tablets, may cause a false-positive reaction for urinary ketone bodies when a test tape is used for determination of ketonuria. This reaction will not be altered by boiling the urine specimen. False-negative tests may result with the use of glucose- oxidase methods of testing for glucosuria.

Cases of falsely diagnosed pheochromocytoma in patients on carbidopa levodopa therapy have been reported very rarely. Caution should be exercised when interpreting the plasma and urine levels of catecholamines and their metabolites in patients on levodopa or carbidopa levodopa therapy.

Drug Interactions

Caution should be exercised when the following drugs are administered concomitantly with carbidopa and levodopa extended-release tablets.

Symptomatic postural hypotension has occurred when carbidopa levodopa preparations were added to the treatment of patients receiving some antihypertensive drugs. Therefore, when therapy with carbidopa and levodopa extended-release tablets is started, dosage adjustment of the antihypertensive drug may be required.

For patients receiving MAO inhibitors (Type A or B), see CONTRAINDICATIONS. Concomitant therapy with selegiline and carbidopa levodopa may be associated with severe orthostatic hypotension not attributable to carbidopa levodopa alone (see CONTRAINDICATIONS).

There have been rare reports of adverse reactions, including hypertension and dyskinesia, resulting from the concomitant use of tricyclic antidepressants and carbidopa levodopa preparations.

Dopamine D2receptor antagonists (e.g., phenothiazines, butyrophenones, risperidone) and isoniazid may reduce the therapeutic effects of levodopa. In addition, the beneficial effects of levodopa in Parkinson's disease have been reported to be reversed by phenytoin and papaverine. Patients taking these drugs with carbidopa and levodopa extended-release tablets should be carefully observed for loss of therapeutic response.

Use of carbidopa and levodopa extended-release tablets with dopamine-depleting agents (e.g., reserpine and tetrabenazine) or other drugs known to deplete monoamine stores is not recommended.

Carbidopa and levodopa extended-release tablets and iron salts or multivitamins containing iron salts should be coadministered with caution. Iron salts can form chelates with levodopa and carbidopa and consequently reduce the bioavailability of carbidopa and levodopa.

Although metoclopramide may increase the bioavailability of levodopa by increasing gastric emptying, metoclopramide may also adversely affect disease control by its dopamine receptor antagonistic properties.

Carcinogenesis, Mutagenesis, Impairment of Fertility

In a two-year bioassay of carbidopa and levodopa tablets, no evidence of carcinogenicity was found in rats receiving doses of approximately two times the maximum daily human dose of carbidopa and four times the maximum daily human dose of levodopa (equivalent to 8 carbidopa and levodopa extended-release tablets).

In reproduction studies with carbidopa and levodopa tablets, no effects on fertility were found in rats receiving doses of approximately two times the maximum daily human dose of carbidopa and four times the maximum daily human dose of levodopa (equivalent to 8 carbidopa and levodopa extended-release tablets).

Pregnancy

No teratogenic effects were observed in a study in mice receiving up to 20 times the maximum recommended human dose of carbidopa and levodopa tablets. There was a decrease in the number of live pups delivered by rats receiving approximately two times the maximum recommended human dose of carbidopa and approximately five times the maximum recommended human dose of levodopa during organogenesis. Carbidopa and levodopa tablets caused both visceral and skeletal malformations in rabbits at all doses and ratios of carbidopa/levodopa tested, which ranged from 10 times/5 times the maximum recommended human dose of carbidopa/levodopa to 20 times/10 times the maximum recommended human dose of carbidopa/levodopa.

There are no adequate or well-controlled studies in pregnant women. It has been reported from individual cases that levodopa crosses the human placental barrier, enters the fetus, and is metabolized. Carbidopa concentrations in fetal tissue appeared to be minimal. Use of carbidopa and levodopa extended-release tablets in women of childbearing potential requires that the anticipated benefits of the drug be weighed against possible hazards to mother and child.

Nursing Mothers

Levodopa has been detected in human milk. Caution should be exercised when carbidopa and levodopa extended-release tablets are administered to a nursing woman.

Pediatric Use

Safety and effectiveness in pediatric patients have not been established. Use of the drug in patients below the age of 18 is not recommended.

Geriatric Use

In the clinical efficacy trials for carbidopa and levodopa tablets, almost half of the patients were older than 65, but few were older than 75. No overall meaningful differences in safety or effectiveness were observed between these subjects and younger subjects, but greater sensitivity of some older individuals to adverse drug reactions such as hallucinations cannot be ruled out. There is no specific dosing recommendation based upon clinical pharmacology data as carbidopa and levodopa tablets and carbidopa and levodopa extended-release tablets are titrated as tolerated for clinical effect.

ADVERSE REACTIONS

In controlled clinical trials, patients predominantly with moderate to severe motor fluctuations while on carbidopa and levodopa tablets were randomized to therapy with either carbidopa and levodopa tablets or carbidopa and levodopa extended-release tablets. The adverse experience frequency profile of carbidopa and levodopa extended-release tablets did not differ substantially from that of carbidopa and levodopa extended-release tablets, as shown in Table 1.

Table 1: Clinical Adverse Experiences Occurring in 1% or Greater of Patients

 | Carbidopa and levodopa extended-release tablets | Carbidopa and levodopa tablets
 | n=491 | n=524
Adverse Experience | % | %
Dyskinesia | 16.5 | 12.2
Nausea | 5.5 | 5.7
Hallucinations | 3.9 | 3.2
Confusion | 3.7 | 2.3
Dizziness | 2.9 | 2.3
Depression | 2.2 | 1.3
Urinary tract infection | 2.2 | 2.3
Headache | 2.0 | 1.9
Dream abnormalities | 1.8 | 0.8
Dystonia | 1.8 | 0.8
Vomiting | 1.8 | 1.9
Upper respiratory infection | 1.8 | 1.0
Dyspnea | 1.6 | 0.4
‘On-Off’ phenomena | 1.6 | 1.1
Back pain | 1.6 | 0.6
Dry mouth | 1.4 | 1.1
Anorexia | 1.2 | 1.1
Diarrhea | 1.2 | 0.6
Insomnia | 1.2 | 1.0
Orthostatic hypotension | 1.0 | 1.1
Shoulder pain | 1.0 | 0.6
Chest pain | 1.0 | 0.8
Muscle cramps | 0.8 | 1.0
Paresthesia | 0.8 | 1.1
Urinary frequency | 0.8 | 1.1
Dyspepsia | 0.6 | 1.1
Constipation | 0.2 | 1.5

Abnormal laboratory findings occurring at a frequency of 1% or greater in approximately 443 patients who received carbidopa and levodopa extended-release tablets and 475 who received carbidopa and levodopa tablets during controlled clinical trials included: decreased hemoglobin and hematocrit; elevated serum glucose; white blood cells, bacteria and blood in the urine.

The adverse experiences observed in patients in uncontrolled studies were similar to those seen in controlled clinical studies.

Other adverse experiences reported overall in clinical trials in 748 patients treated with carbidopa and levodopa extended-release tablets, listed by body system in order of decreasing frequency, include:

Body as a Whole

Asthenia, fatigue, abdominal pain, orthostatic effects.

Cardiovascular

Palpitation, hypertension, hypotension, myocardial infarction.

Gastrointestinal

Gastrointestinal pain, dysphagia, heartburn.

Metabolic

Weight loss.

Musculoskeletal

Leg pain.

Nervous System/Psychiatric

Chorea, somnolence, falling, anxiety, disorientation, decreased mental acuity, gait abnormalities, extrapyramidal disorder, agitation, nervousness, sleep disorders, memory impairment.

Respiratory

Cough, pharyngeal pain, common cold.

Skin

Rash.

Special Senses

Blurred vision.

Urogenital

Urinary incontinence.

Laboratory Tests

Decreased white blood cell count and serum potassium; increased BUN, serum creatinine and serum LDH; protein and glucose in the urine.

The following adverse experiences have been reported in postmarketing experience with carbidopa and levodopa extended-release tablets:

Cardiovascular

Cardiac irregularities, syncope.

Gastrointestinal

Taste alterations, dark saliva.

Hypersensitivity

Angioedema, urticaria, pruritus, bullous lesions (including pemphigus-like reactions).

Nervous System/Psychiatric

Increased tremor, peripheral neuropathy, psychotic episodes including delusions and paranoid ideation, pathological gambling, increased libido including hypersexuality, impulse control symptoms.

Skin

Alopecia, flushing, dark sweat.

Urogenital

Dark urine.

Other adverse reactions that have been reported with levodopa alone and with various carbidopa levodopa formulations and may occur with carbidopa and levodopa extended-release tablets are:

Cardiovascular

Phlebitis.

Gastrointestinal

Gastrointestinal bleeding, development of duodenal ulcer, sialorrhea, bruxism, hiccups, flatulence, burning sensation of tongue.

Hematologic

Hemolytic and non-hemolytic anemia, thrombocytopenia, leukopenia, agranulocytosis.

Hypersensitivity

Henoch-Schönlein purpura.

Metabolic

Weight gain, edema.

Nervous System/Psychiatric

Ataxia, depression with suicidal tendencies, dementia, euphoria, convulsions (however, a causal relationship has not been established); bradykinetic episodes, numbness, muscle twitching, blepharospasm (which may be taken as an early sign of excess dosage; consideration of dosage reduction may be made at this time), trismus, activation of latent Horner's syndrome, nightmares.

Skin

Malignant melanoma (see also CONTRAINDICATIONS), increased sweating.

Special Senses

Oculogyric crises, mydriasis, diplopia.

Urogenital

Urinary retention, priapism.

Miscellaneous

Faintness, hoarseness, malaise, hot flashes, sense of stimulation, bizarre breathing patterns.

Laboratory Tests

Abnormalities in alkaline phosphatase, SGOT (AST), SGPT (ALT), bilirubin, Coombs test, uric acid.

To report SUSPECTED ADVERSE REACTIONS, contact Advagen Pharma Ltd, at 866-488-0312 or FDA at 1-800-FDA-1088 or www.fda.gov/medwatch.

OVERDOSAGE

Management of acute overdosage with carbidopa and levodopa extended-release tablets is the same as with levodopa. Pyridoxine is not effective in reversing the actions of carbidopa and levodopa extended-release tablets.

General supportive measures should be employed, along with immediate gastric lavage. Intravenous fluids should be administered judiciously and an adequate airway maintained. Electrocardiographic monitoring should be instituted and the patient carefully observed for the development of arrhythmias; if required, appropriate antiarrhythmic therapy should be given. The possibility that the patient may have taken other drugs as well as carbidopa and levodopa extended-release tablets should be taken into consideration. To date, no experience has been reported with dialysis; hence, its value in overdosage is not known.

Based on studies in which high doses of levodopa and/or carbidopa were administered, a significant proportion of rats and mice given single oral doses of levodopa of approximately 1500-2000 mg/kg are expected to die. A significant proportion of infant rats of both sexes are expected to die at a dose of 800 mg/kg. A significant proportion of rats are expected to die after treatment with similar doses of carbidopa. The addition of carbidopa in a 1:10 ratio with levodopa increases the dose at which a significant proportion of mice are expected to die to 3360 mg/kg.

DOSAGE AND ADMINISTRATION

Carbidopa and levodopa extended-release tablet contains carbidopa and levodopa in a 1:4 ratio as either the 50 mg/200 mg tablet or the 25 mg/100 mg tablet. The daily dosage of carbidopa and levodopa extended-release tablets must be determined by careful titration. Patients should be monitored closely during the dose adjustment period, particularly with regard to appearance or worsening of involuntary movements, dyskinesias or nausea. Carbidopa and levodopa extended-release tablets should not be chewed or crushed.

Standard drugs for Parkinson's disease, other than levodopa without a decarboxylase inhibitor, may be used concomitantly while carbidopa and levodopa extended-release tablet is being administered, although their dosage may have to be adjusted.

Since carbidopa prevents the reversal of levodopa effects caused by pyridoxine, carbidopa and levodopa extended-release tablets can be given to patients receiving supplemental pyridoxine (vitamin B6).

Initial Dosage

Patients currently treated with conventional carbidopa levodopa preparations: Studies show that peripheral dopa-decarboxylase is saturated by the bioavailable carbidopa at doses of 70 mg a day and greater. Because the bioavailabilities of carbidopa and levodopa in carbidopa and levodopa tablets and carbidopa and levodopa extended-release tablets are different, appropriate adjustments should be made, as shown in Table 2.

Table 2: Approximate Bioavailabilities at Steady State*

Tablet | Amount of Levodopa (mg) in Each Tablet | Approximate Bioavailability | Approximate Amount of Bioavailable Levodopa (mg) in Each Tablet
Carbidopa and levodopa extended-release tablets 50 mg/ 200 mg | 200 | 0.70-0.75† | 140-150
Carbidopa and levodopa tablets 25 mg/ 100 mg | 100 | 0.99‡ | 99

* This table is only a guide to bioavailabilities since other factors such as food, drugs, and inter-patient variabilities may affect the bioavailability of carbidopa and levodopa.

†The extent of availability of levodopa from carbidopa and levodopa extended-release tablets was about 70-75% relative to intravenous levodopa or standard carbidopa and levodopa tablets in the elderly.

‡ The extent of availability of levodopa from carbidopa and levodopa tablets was 99% relative to intravenous levodopa in the healthy elderly.

Dosage with carbidopa and levodopa extended-release tablets should be substituted at an amount that provides approximately 10% more levodopa per day, although this may need to be increased to a dosage that provides up to 30% more levodopa per day depending on clinical response (see DOSAGE AND ADMINISTRATION, Titration with carbidopa and levodopa extended-release tablets). The interval between doses of carbidopa and levodopa extended-release tablets should be 4-8 hours during the waking day. (See CLINICAL PHARMACOLOGY, Pharmacodynamics.)

A guideline for initiationof carbidopa and levodopa extended-release tablets is shown in Table 3.

Table 3: Guidelines for Initial Conversion from Carbidopa and Levodopa Tablets to Carbidopa and Levodopa Extended-Release Tablets

Carbidopa and levodopa tablets | Carbidopa and levodopa extended-release tablets
Total Daily Dose* | Suggested
Levodopa (mg) | Dosage Regimen
300-400 | 200 mg b.i.d.
500-600 | 300 mg b.i.d. or 200 mg t.i.d.
700-800 | A total of 800 mg in 3 or more divided doses (e.g., 300 mg a.m., 300 mg early p.m., and 200 mg later p.m.)
900-1000 | A total of 1000 mg in 3 or more divided doses (e.g., 400 mg a.m., 400 mg early p.m., and 200 mg later p.m.)

*For dosing ranges not shown in the table see DOSAGE AND ADMINISTRATION, Initial Dosage — Patients currently treated with conventional carbidopa levodopa preparations.

Patients currently treated with levodopa without a decarboxylase inhibitor:Levodopa must be discontinued at least twelve hours before therapy with carbidopa and levodopa extended-release tablets is started. Carbidopa and levodopa extended-release tablets should be substituted at a dosage that will provide approximately 25% of the previous levodopa dosage. In patients with mild to moderate disease, the initial dose is usually 1 tablet of carbidopa and levodopa extended-release tablets 50 mg/200 mg b.i.d.

Patients not receiving levodopa:In patients with mild to moderate disease, the initial recommended dose is 1 tablet of carbidopa and levodopa extended-release tablets 50 mg/200 mg b.i.d. Initial dosage should not be given at intervals of less than 6 hours.

Titration with Carbidopa and Levodopa Extended-Release Tablets

Following initiation of therapy, doses and dosing intervals may be increased or decreased depending upon therapeutic response. Most patients have been adequately treated with doses of carbidopa and levodopa extended-release tablets that provide 400 to 1600 mg of levodopa per day, administered as divided doses at intervals ranging from 4 to 8 hours during the waking day. Higher doses of carbidopa and levodopa extended-release tablets (2400 mg or more of levodopa per day) and shorter intervals (less than 4 hours) have been used, but are not usually recommended.

When doses of carbidopa and levodopa extended-release tablets are given at intervals of less than 4 hours, and/or if the divided doses are not equal, it is recommended that the smaller doses be given at the end of the day.

An interval of at least 3 days between dosage adjustments is recommended.

Maintenance

Because Parkinson's disease is progressive, periodic clinical evaluations are recommended; adjustment of the dosage regimen of carbidopa and levodopa extended-release tablets may be required.

Addition of Other Antiparkinson Medications

Anticholinergic agents, dopamine agonists, and amantadine can be given with carbidopa and levodopa extended-release tablets. Dosage adjustment of carbidopa and levodopa extended-release tablets may be necessary when these agents are added.

A dose of carbidopa levodopa tablets 25 mg/100 mg or 10 mg/100 mg(one half or a whole tablet) can be added to the dosage regimen of carbidopa and levodopa extended-release tablets in selected patients with advanced disease who need additional immediate-release levodopa for a brief time during daytime hours.

Interruption of Therapy

Sporadic cases of hyperpyrexia and confusion have been associated with dose reductions and withdrawal of carbidopa and levodopa tablets or carbidopa and levodopa extended-release tablets. Patients should be observed carefully if abrupt reduction or discontinuation of carbidopa and levodopa extended-release tablets is required, especially if the patient is receiving neuroleptics. (See WARNINGS.)

If general anesthesia is required, carbidopa and levodopa extended-release tablets may be continued as long as the patient is permitted to take oral medication. If therapy is interrupted temporarily, the patient should be observed for symptoms resembling NMS, and the usual dosage should be administered as soon as the patient is able to take oral medication.

HOW SUPPLIED

Carbidopa and levodopa extended-release tablets, USP 25 mg/100 mg are light purple to purple, dappled, oval, uncoated tablets, debossed with “Λ50” on one side and plain on other. They are supplied as follows:

NDC 72888-155-30, bottles of 30.

NDC 72888-155-01, bottles of 100.

NDC 72888-155-05, bottles of 500.

NDC 72888-155-00, bottles of 1000.

Carbidopa and levodopa extended-release tablets, USP 50 mg/200 mg are light purple to purple, dappled, oval, uncoated tablets, debossed with “Λ51” on one side and plain on other. They are supplied as follows:

NDC 72888-156-30, bottles of 30.

NDC 72888-156-01, bottles of 100.

NDC 72888-156-05, bottles of 500.

NDC 72888-156-00, bottles of 1000.

Storage and Handling

Store at 25°C (77°F); excursions permitted to 15° to 30°C (59° to 86°F) [see USP Controlled Room Temperature]. Store in a tightly closed container, protected from light and moisture.

Dispense in a tightly closed, light-resistant container.

All trademarks are the property of their respective owners.

Manufactured by:

Rubicon Research Limited

Thane 421506, India

Distributed by:

Advagen Pharma Ltd.,

East Windsor, NJ 08520, USA

Revision: 12/2025

PACKAGE LABEL.PRINCIPAL DISPLAY PANEL

Carbidopa and Levodopa Extended-Release Tablets, USP 25 mg/100 mg - NDC 72888-155-30 - 30 Tablets Label

Carbidopa and Levodopa Extended-Release Tablets, USP 25 mg/100 mg - NDC 72888-155-01 - 100 Tablets Label

Carbidopa and Levodopa Extended-Release Tablets, USP 25 mg/100 mg - NDC 72888-155-05 - 500 Tablets Label

Carbidopa and Levodopa Extended-Release Tablets, USP 25 mg/100 mg - NDC 72888-155-00 - 1000 Tablets Label

Carbidopa and Levodopa Extended-Release Tablets, USP 50 mg/200 mg - NDC 72888-156-30 - 30 Tablets Label

Carbidopa and Levodopa Extended-Release Tablets, USP 50 mg/200 mg - NDC 72888-156-01 - 100 Tablets Label

Carbidopa and Levodopa Extended-Release Tablets, USP 50 mg/200 mg - NDC 72888-156-05 - 500 Tablets Label

Carbidopa and Levodopa Extended-Release Tablets, USP 50 mg/200 mg - NDC 72888-156-00 - 1000 Tablets Label